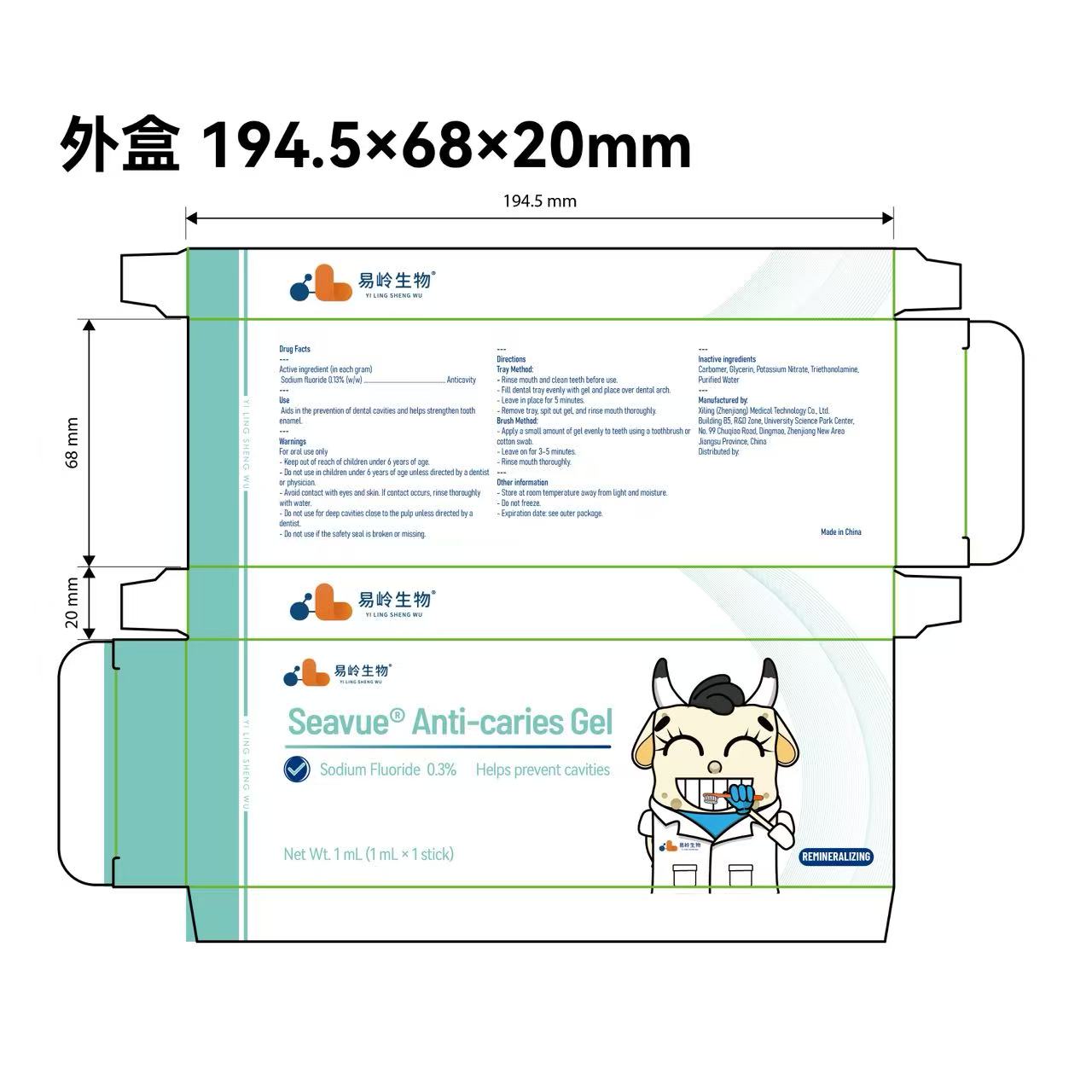 DRUG LABEL: Seavue Anti-caries Gel
NDC: 87118-004 | Form: GEL
Manufacturer: Xiling (Zhenjiang) Medical Technology Co., Ltd.
Category: otc | Type: HUMAN OTC DRUG LABEL
Date: 20250921

ACTIVE INGREDIENTS: SODIUM FLUORIDE 1.36 mg/1 g
INACTIVE INGREDIENTS: CARBOMER; GLYCERIN; TRIETHANOLAMINE; WATER; POTASSIUM NITRATE

ACTIVE INGREDIENT

Sodium Fluoride

Do not use in children under 6 years of age unless directed by a dentist or physician.

Do not use for deep cavities close to the pulp unless directed by a dentist.

Do not use if the safety seal is broken or missing.

Keep out of reach of children under 6 years of age.

PURPOSE

Anticavity

WHEN USING

Tray Method:

Rinse mouth and clean teeth before use.
Fill dental tray evenly with gel and place over dental arch.
Leave in place for 5 minutes.
Remove tray, spit out gel, and rinse mouth thoroughly.

Brush Method:

Apply a small amount of gel evenly to teeth using a toothbrush or cotton swab.
Leave on for 3–5 minutes.
Rinse mouth thoroughly.

DOSAGE AND ADMINISTRATION

Sodium fluoride 0.3% (w/w)
Aids in the prevention of dental cavities and helps strengthen tooth enamel.

WARNINGS

For oral use only

Keep out of reach of children under 6 years of age.
Do not use in children under 6 years of age unless directed by a dentist or physician.
Avoid contact with eyes and skin. If contact occurs, rinse thoroughly with water.
Do not use for deep cavities close to the pulp unless directed by a dentist.
Do not use if the safety seal is broken or missing.

INACTIVE INGREDIENT

Carbomer, Glycerin, Potassium Nitrate, Triethanolamine, Purified Water

Directions
Tray Method:

Rinse mouth and clean teeth before use.
Fill dental tray evenly with gel and place over dental arch.
Leave in place for 5 minutes.
Remove tray, spit out gel, and rinse mouth thoroughly.

Brush Method:

Apply a small amount of gel evenly to teeth using a toothbrush or cotton swab.
Leave on for 3–5 minutes.
Rinse mouth thoroughly.